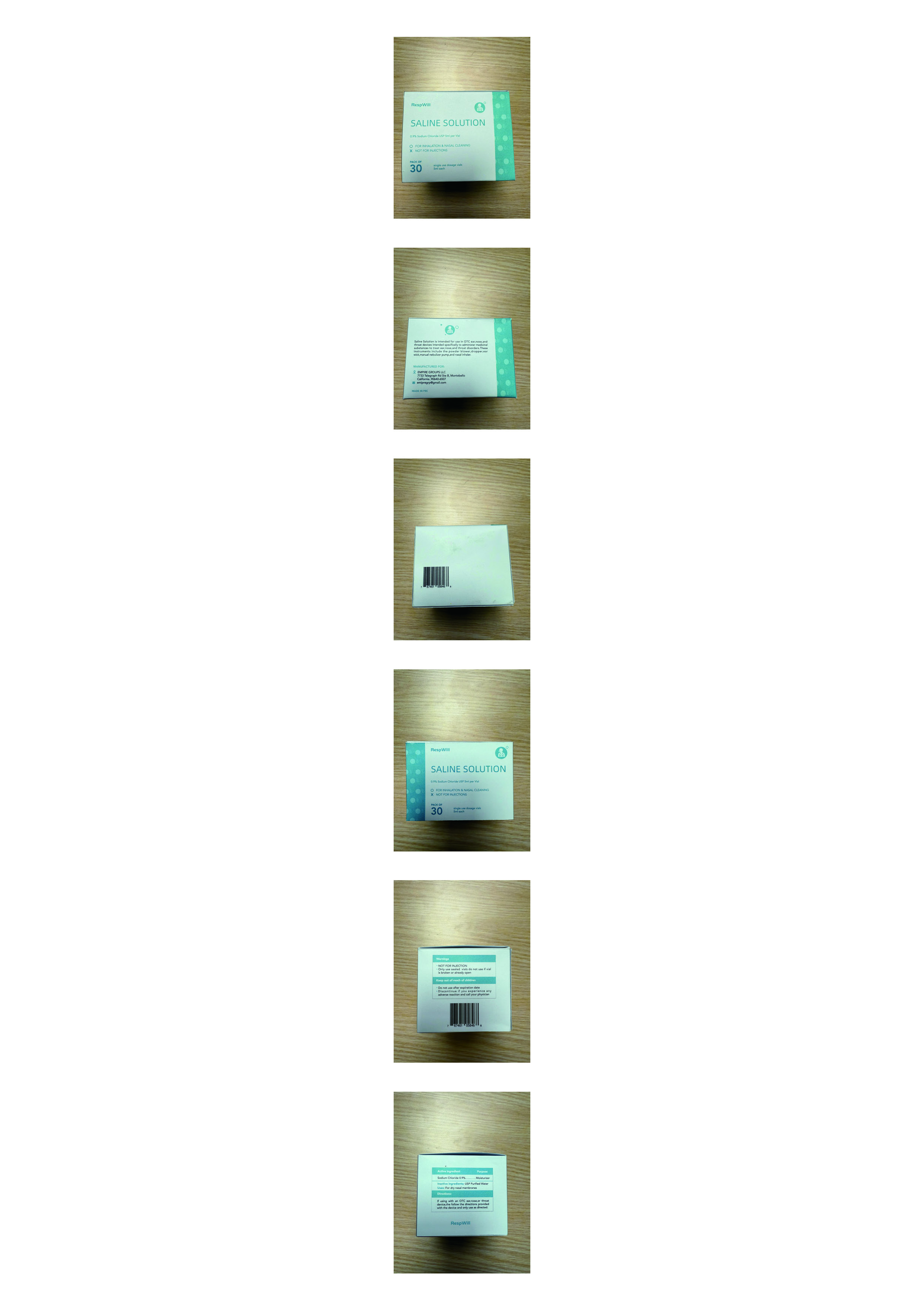 DRUG LABEL: 0.9 percent saline solution
NDC: 85602-101 | Form: LIQUID
Manufacturer: EMPIRE GROUPS LLC
Category: otc | Type: HUMAN OTC DRUG LABEL
Date: 20250430

ACTIVE INGREDIENTS: SODIUM CHLORIDE 9 mg/1 mL
INACTIVE INGREDIENTS: WATER

0.9 percent saline solution

Active ingredien: Sodium Chloride 0.9%

Inactive ingredien: USP Water

WARNINGS

Warings:

NOT FOR INJECTION;

Only use sealed vials do not use if vialis broken or already open

Keep out of reach of children:
Do not use after expiration date;
Discontinue if you experience any adverse reaction and call your physician

Single use dosage vials 5ml each

INDICATIONS AND USAGE

Saline Solution is intended for use in OTC ear,nose,and throat devices intended specifically to administer medicinal substances to treat ear,nose,and throat disorders.These instruments include the powder blower,dropper,ear wick,manual nebulizer pump,and nasal inhaler.

If using with an OTC ear,nose,or throat device,the follow the directions provided with the device and only use as directed.

PURPOSE

Uses: Moisturizer

For dry nasal membranes

QUESTIONS

Question:

emipregrp@gmail.com

See Label